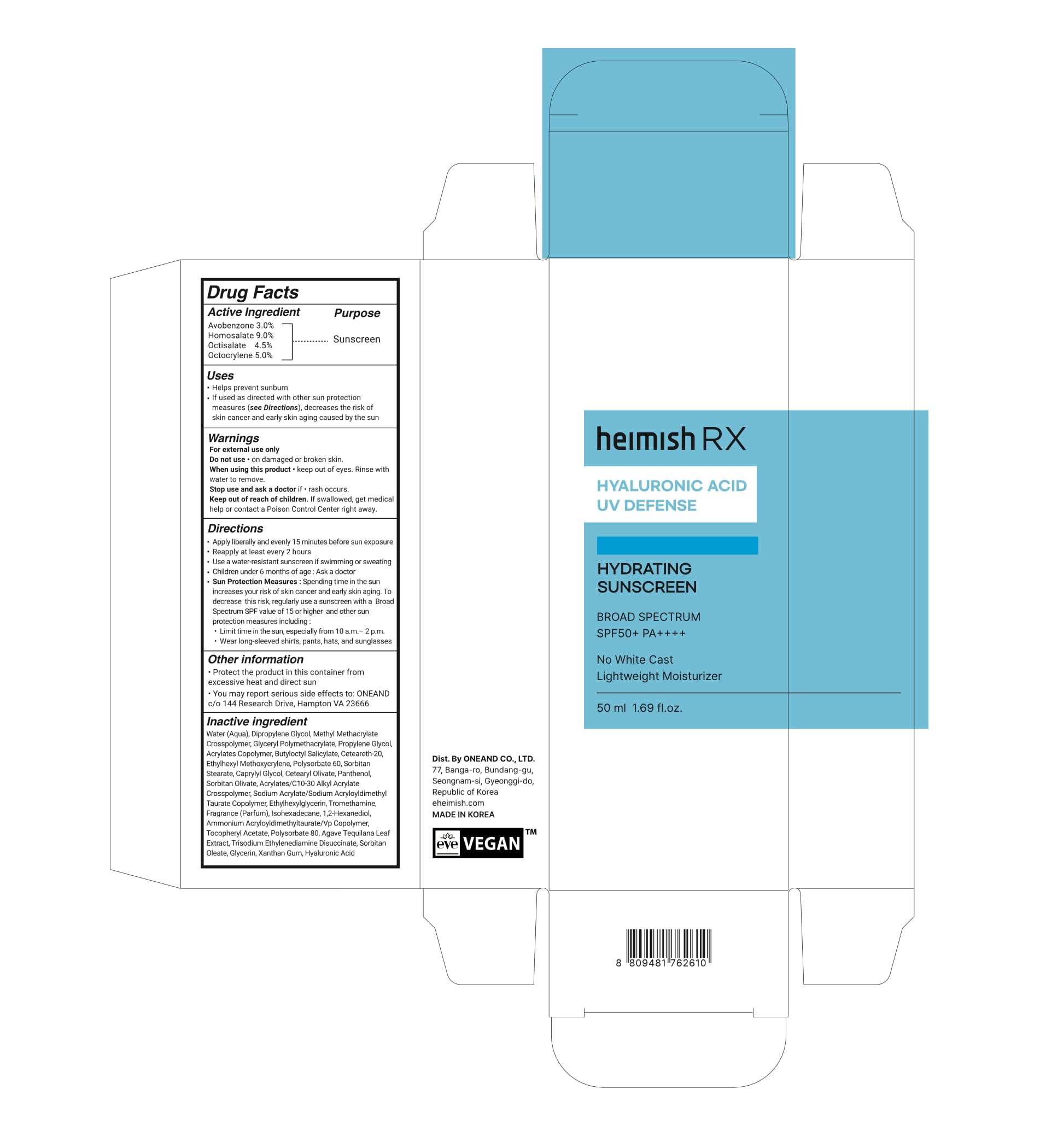 DRUG LABEL: HEIMISH RX HYALURONIC ACID HYDRATING SUNSCREEN
NDC: 85315-001 | Form: LOTION
Manufacturer: ONEAND CO., LTD.
Category: otc | Type: HUMAN OTC DRUG LABEL
Date: 20251113

ACTIVE INGREDIENTS: HOMOSALATE 4.5 g/50 mL; OCTOCRYLENE 2.5 g/50 mL; AVOBENZONE 1.5 g/50 mL; OCTISALATE 2.25 g/50 mL
INACTIVE INGREDIENTS: WATER; SODIUM ACRYLATE/SODIUM ACRYLOYLDIMETHYLTAURATE COPOLYMER (4000000 MW); BUTYLOCTYL SALICYLATE; ETHYLHEXYLGLYCERIN; CAPRYLYL GLYCOL; ISOHEXADECANE; 1,2-HEXANEDIOL; GLYCERYL POLYMETHACRYLATE (300000 MPA.S); METHYL METHACRYLATE/GLYCOL DIMETHACRYLATE CROSSPOLYMER; PROPYLENE GLYCOL; CARBOMER 1342; DIPROPYLENE GLYCOL; SORBITAN STEARATE; CETEARYL OLIVATE; PANTHENOL; CETEARETH-20; POLYSORBATE 60; SORBITAN OLIVATE; TROMETHAMINE; BUTYL ACRYLATE/METHYL METHACRYLATE/METHACRYLIC ACID COPOLYMER (18000 MW); ETHYLHEXYL METHOXYCRYLENE

85315-001 HEIMISH RX HYALURONIC ACID HYDRATING SUNSCREEN

ACTIVE INGREDIENT

Avobenzone 3.0%

Homosalate 9.0%

Octisalate 4.5%

Octocrylene 5.0%

PURPOSE

Sunscreen

INDICATIONS AND USAGE

● Helps prevent sunburn

● If used as directed with other sun protection measures (see Directions), decreases the risk of skin cancer and early skin aging caused by the sun.

WARNINGS

For external use only

Do not use ● on damaged or broken skin

When using this product ● keep out of eyes.Rinse with water to remove.

Stop use and ask a doctor if ● rash occurs

Keep out of reach of children. If swallowed, get medical help or contact a Poison Control Center right away.

OTHER SAFETY INFORMATION

● Protect the product in this container from excessive heat and direct sun.

● You may report serious side effects to: ONEAND c/o 144 Research Drive, Hampton VA 23666

DOSAGE AND ADMINISTRATION

● Apply liberally and evenly 15 minutes before sun exposure

● Reapply at least every 2 hours
● Use a water-resistant sunscreen if swimming or sweating

● Children under 6 months of age: Ask a doctor
● Sun Protection Measures: Spending time in the sun increases your risk of skin cancer and early skin aging. To decrease this risk, regularly use a sunscreen with a Broad Spectrum SPF value of 15 or higher and other sun
protection measures including:
● Limit time in the sun, especially from 10a.m.-2 p.m.

● Wear long-sleeved shirts, pants, hats, and sunglasses

INACTIVE INGREDIENT

Water (Aqua), Dipropylene Glycol, Methyl Methacrylate Crosspolymer, Glyceryl Polymethacrylate, Propylene Glycol, Acrylates Copolymer, Butyloctyl Salicylate, Ceteareth-20, Ethylhexyl Methoxycrylene, Polysorbate 60, Sorbitan Stearate, Caprylyl Glycol, Cetearyl Olivate, Panthenol, Sorbitan Olivate, Acrylates/C10-30 Alkyl Acrylate Crosspolymer, Sodium Acrylate/Sodium Acryloyldimethyl Taurate Copolymer, Ethylhexylglycerin, Tromethamine, Fragrance (Parfum), Isohexadecane, 1,2-Hexanediol, Ammonium Acryloyldimethyltaurate/Vp Copolymer, Tocopheryl Acetate, Polysorbate 80, Agave Tequilana Leaf Extract, Trisodium Ethylenediamine Disuccinate, Sorbitan Oleate, Glycerin, Xanthan Gum, Hyaluronic Acid